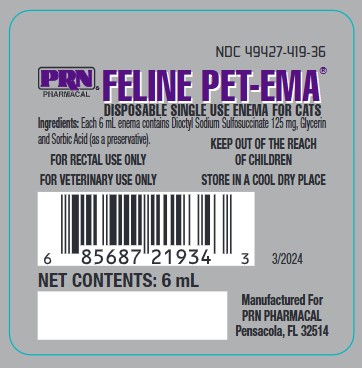 DRUG LABEL: FELINE PET-EMA
								
NDC: 49427-419 | Form: ENEMA
Manufacturer: Pegasus Laboratories, Inc
Category: animal | Type: OTC ANIMAL DRUG LABEL
Date: 20251229

ACTIVE INGREDIENTS: DOCUSATE SODIUM 125 mg/6 mL

FELINE PET-EMA

Disposable Single Use Enema for Cats

Each 6 mL enema contains Dioctyl Sodium Sulfosuccinate 125 mg in Glycerin, with Sorbic Acid (as a preservative).

Stimulates the mucosa of the lower bowel and rectum; softens hardened fecal matter; lubricates the rectal wall.

USES:

As an aid in maintaining healthy lower bowel function.

DIRECTIONS FOR USE:

Remove tip cap and gently insert nozzle into rectum. If desired, nozzle can be lubricated prior to insertion. Slowly depress syringe plunger to express contents. Treatment may be repeated in one hour if necessary.

PRECAUTIONS

For rectal use only

For veterinary use only

Keep out of reach of children

Store in a cool dry place

PACKAGE LABEL

NDC 49427-419-36
PRN PHARMACAL FELINE PET-EMA
Disposable Single Use Enema for Cats
Manufactured For PRN PHARMACAL
Pensacola, FL 32514
NET CONTENTS: 6mL